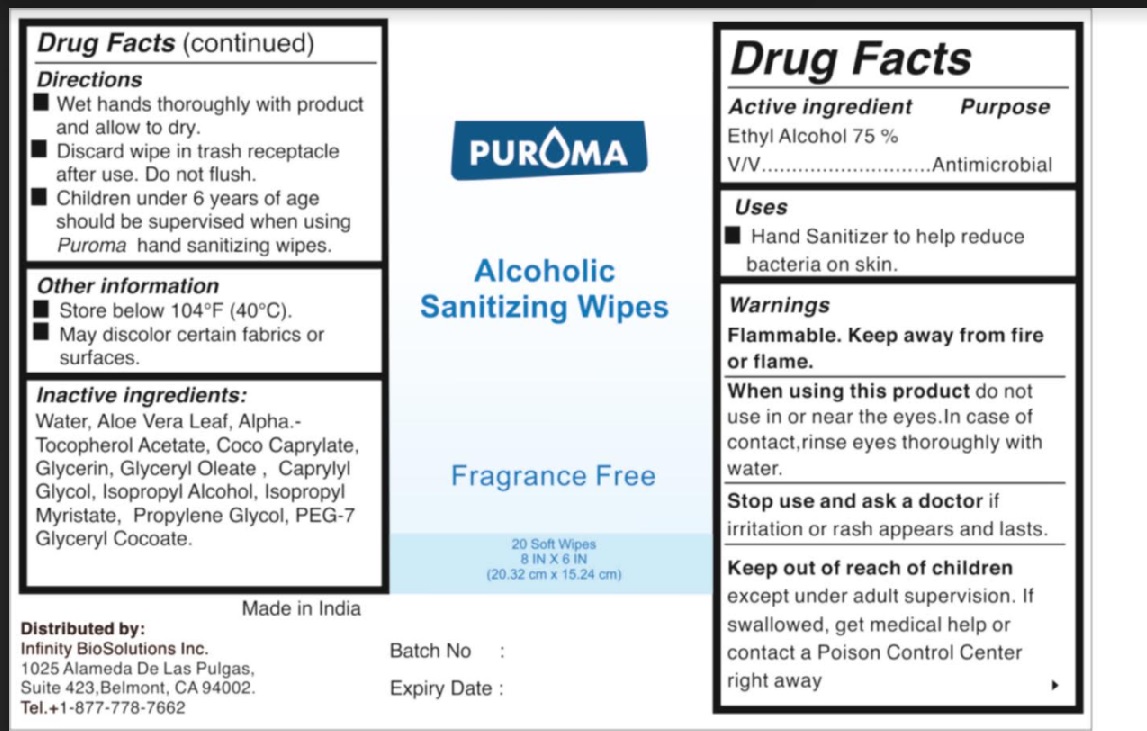 DRUG LABEL: PUROMA  Alcohol Hand Sanitizer Wipes  Fragrance Free
NDC: 80948-004 | Form: CLOTH
Manufacturer: ZENITH MICRO CONTROL
Category: otc | Type: HUMAN OTC DRUG LABEL
Date: 20231213

ACTIVE INGREDIENTS: ALCOHOL 75 mL/100 mL
INACTIVE INGREDIENTS: WATER; ISOPROPYL ALCOHOL; GLYCERIN; ISOPROPYL MYRISTATE; .ALPHA.-TOCOPHEROL ACETATE; CAPRYLYL GLYCOL; ALOE VERA LEAF; PROPYLENE GLYCOL; COCO-CAPRYLATE; GLYCERYL OLEATE; PEG-7 GLYCERYL COCOATE

Active ingredient

Ethyl alcohol 75% V/V

Purpose

Antimicrobial.

Uses

Hand Sanitizer to help reduce bacteria on skin.

Warnings

Flammable. Keep away from fire or flame.
For external use only.
When using this product do not use in or near the eyes. In case of contact, rinse eyes thoroughly with water.
Stop use and ask a doctor if irritation or rash appears and lasts.

Keep out of reach of children

except under adult supervision. If swallowed, get medical help or contact a Poison Control Center right away.

Directions

Wet hands thoroughly with product and allow to dry.
Discard wipe in trash receptacle after use. Do not flush.
Children under 6 years of age should be supervised when using Puroma Hand Sanitizer wipe.

Inactive ingredients

Water,Isopropyl Alcohol ,Glycerin, Isopropyl Myristate, Alpha.- Tocopherol Acetate , Caprylyl Glycol, Aloe Vera Leaf, Propylene Glycol, Coco-Caprylate , PEG-7 Glyceryl Cocoate, Glyceryl Oleate

Other information

Store below 110°F (40°C).
May discolor certain fabrics or surfaces.